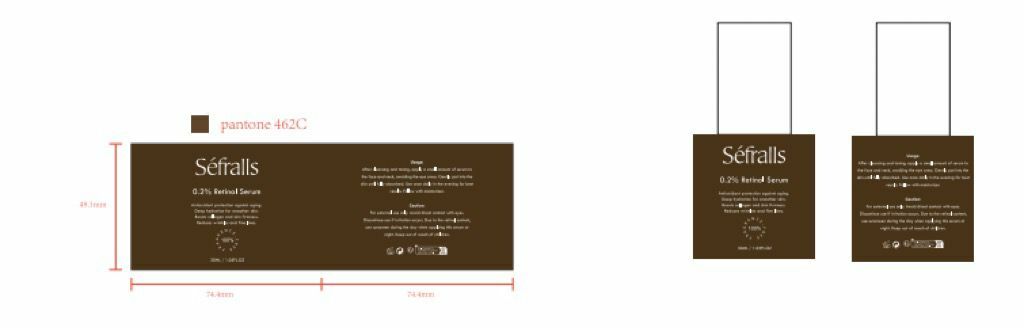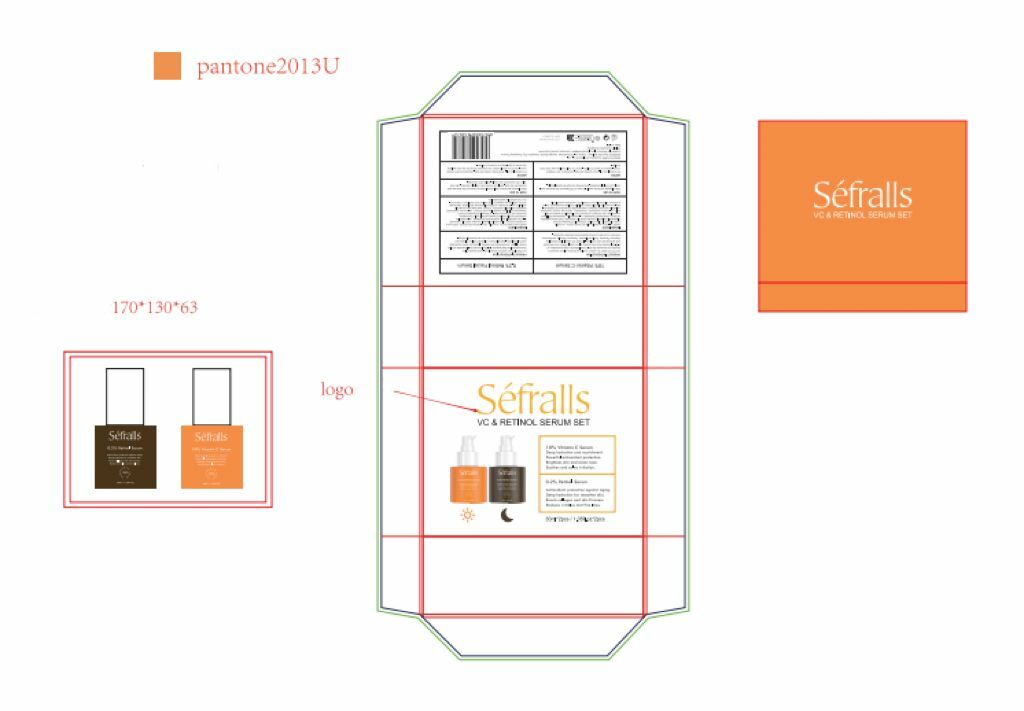 DRUG LABEL: 2-Pack Facial Serum
NDC: 84148-012 | Form: LIQUID
Manufacturer: Guangzhou Ariel Biotech Co., Ltd.
Category: otc | Type: HUMAN OTC DRUG LABEL
Date: 20241125

ACTIVE INGREDIENTS: 3-O-ETHYL ASCORBIC ACID 0.5 g/100 mL; HYDROXYPINACOLONE RETINOATE 0.2 g/100 mL; TARAXACUM OFFICINALE LEAF 0.005 g/100 mL; PURSLANE 0.07 g/100 mL
INACTIVE INGREDIENTS: SIMMONDSIA CHINENSIS (JOJOBA) SEED OIL; HYDROXYACETOPHENONE; HYDROXYETHYLPIPERAZINE ETHANE SULFONIC ACID; POLYACRYLATE CROSSPOLYMER-6; HYDROGENATED SOYBEAN LECITHIN; TOCOPHEROL; C20-22 ALKYL PHOSPHATE; XANTHAN GUM; ALLANTOIN; WATER; ARGININE; C20-22 ALCOHOLS; SODIUM HYALURONATE; DIPOTASSIUM GLYCYRRHIZATE; BUTYLENE GLYCOL; GLYCERIN; COCO-CAPRYLATE/CAPRATE; DIMETHYL ISOSORBIDE; 1,2-HEXANEDIOL; SQUALANE

84148-012

Active Ingredient(s)

3-o-ETHYL ASCORBIC ACID 0.500%

PORTULACA OLERACEA EXTRACT 0.070

SAURURUS CHINENSIS LEAF/ROOT EXTRACT 0.005%

TARAXACUM OFFICINALE (DANDELION) LEAF EXTRACT 0.005%

STEPHANIA TETRANDRA EXTRACT 0.001%

HYDROXYPINACOLONE RETINOATE 0.200%

Purpose

Anti aging, promotes collagen, enhances skin radiance

Use

After cleansing and toning, apply a small amount of serum to the face and neck,
avoiding the eye area. Gently pat into the skin until fully absorbed, Use once
daily in the evening for best results. Follow with moisturizer.

Warnings

For external use only. Avoid direct contact with eyes. Discontinue use if irritation
occurs. Due to the retinol content, use sunscreen during the day when applying
this serum at night. Keep out of reach of children.

Do not use

If there is any irritation, please stop using immediately

WHEN USING

When Using Section: When using this product, avoid contact with eyes. If contact occurs,
rinse thoroughly with water. Discontinve use if any irritation or adverse reaction occurs.

STOP USE

For external use only. Avoid direct contact with eyes. Discontinue use if irritation
occurs. Due to the retinol content, use sunscreen during the day when applying
this serum at night. Keep out of reach of children.

Keep out of reach of children.

Directions

Because it contains retinal ingredients, sunscreen should be used in the daytime when using this essence at night

Other information

No Data

Inactive ingredients

POLYACRYLATE CROSSPOLYMER-6，HYDROGENATED LECITHIN，TOCOPHEROL，C20-22 ALKYL PHOSPHATE，

XANTHAN GUM，ALLANTOIN，WATER，ARGININE，C20-22 ALCOHOLS，SODIUM HYALURONATE，

DIPOTASSIUM GLYCYRRHIZATE，BUTYLENE GLYCOL，GLYCERIN，COCO-CAPRYLATE/CAPRATE，

DIMETHYL ISOSORBIDE，SIMMONDSIA CHINENSIS (JOJOBA) SEED OIL，SQUALANE，1,2-HEXANEDIOL，

HYDROXYACETOPHENONE，HYDROXYETHYLPIPERAZINE ETHANE SULFONIC ACID